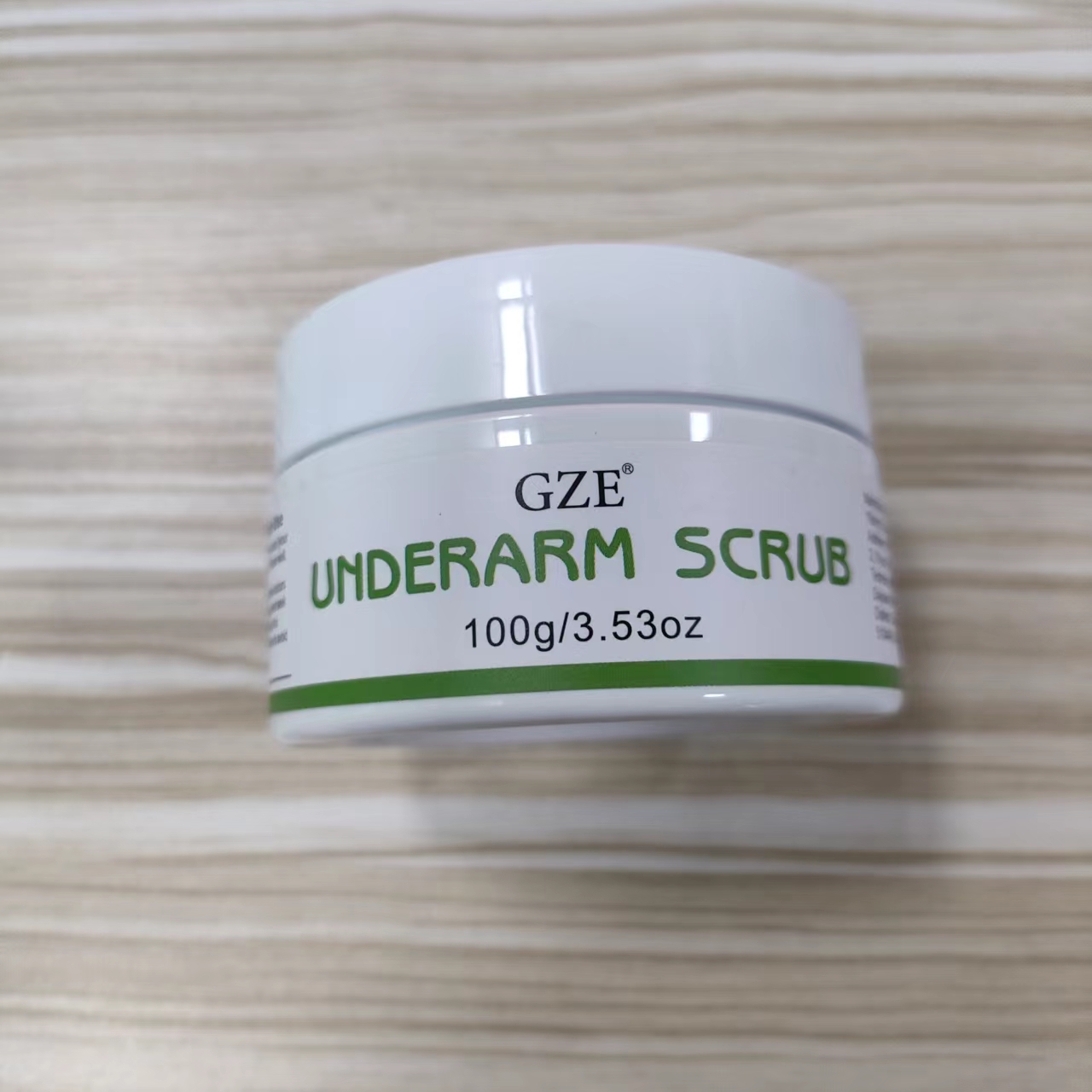 DRUG LABEL: GZE UNDERARM SCRUB
NDC: 74458-226 | Form: GRANULE
Manufacturer: Guangzhou Yilong Cosmetics Co., Ltd
Category: otc | Type: HUMAN OTC DRUG LABEL
Date: 20241107

ACTIVE INGREDIENTS: MENTHOL 1.45 g/100 g
INACTIVE INGREDIENTS: AQUA; CARBOMER; CI 42090; ALOE BARBADENSIS LEAF EXTRACT; CI 19140; POLYSORBATE 60; JUGLANS REGIA SHELL; MINERAL OIL; SODIUM CHLORIDE

GZE UNDERARM SCRUB

ACTIVE INGREDIENT

Menthol

INACTIVE INGREDIENT

Aqua

Mineral Oil

Aloe Barbadensis Leaf Extract

Juglans Regia (Walnut)Shell Powder

Polysorbate 60

Carbomer

Sodium Chloride

CI 19140

CI 42090

PURPOSE

Exfoliation.

INDICATIONS AND USAGE

Wet your body and scoop out the scrub and apply to your underarms, rubbing in circular motions for 2-3 minutes and rinse off with water.

PURPOSE

For external use only.

Stop use and ask a doctor if rash occurs.

Do not use on damaged or broken skin.

When using this product keep out of eyes. Rinse with water to remove.

Keep out of reach of children. If swallowed, get medical help or contact a Poison Control Center right away.

DOSAGE AND ADMINISTRATION

Wet your body and scoop out the scrub and apply to your underarms, rubbing in circular motions for 2-3 minutes and rinse off with water.